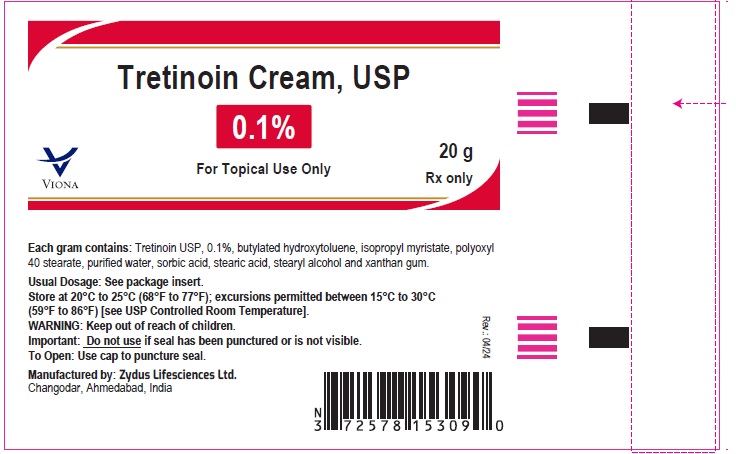 DRUG LABEL: Tretinoin
NDC: 70771-1873 | Form: CREAM
Manufacturer: Zydus Lifesciences Limited
Category: prescription | Type: HUMAN PRESCRIPTION DRUG LABEL
Date: 20240426

ACTIVE INGREDIENTS: TRETINOIN 1 mg/1 g
INACTIVE INGREDIENTS: BUTYLATED HYDROXYTOLUENE; ISOPROPYL MYRISTATE; POLYOXYL 40 STEARATE; SORBIC ACID; STEARIC ACID; STEARYL ALCOHOL; WATER; XANTHAN GUM

Tretinoin Cream, USP

PACKAGE LABEL.PRINCIPAL DISPLAY PANEL

NDC 70771-1873-2

Tretinoin cream USP, 0.1%

20 grams

Rx